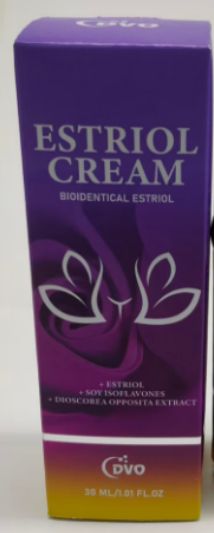 DRUG LABEL: DVO Estriol cream
NDC: 87204-503 | Form: CREAM
Manufacturer: Guangzhou Huixue Biotechnology Co., Ltd.
Category: otc | Type: HUMAN OTC DRUG LABEL
Date: 20251105

ACTIVE INGREDIENTS: ESTRIOL 0.2 g/30 mL
INACTIVE INGREDIENTS: TOCOPHEROL; HYALURONIC ACID; GLYCERIN; SIMMONDSIA CHINENSIS (JOJOBA) SEED OIL; SOY ISOFLAVONES; VITIS VINIFERA (GRAPE) SEED OIL; WATER; CAMELLIA JAPONICA SEED OIL; BUTYROSPERMUM PARKII (SHEA) OIL; CETEARYL ALCOHOL; PANTHENOL

ACTIVE INGREDIENT

ESTRIOL0.2%

PURPOSE

Supplement estrogen to alleviate inflammation

INDICATIONS AND USAGE

1. Clean the affected area of the skin.
2. Apply 1-2ml in the area where it is needed.
3. Spread it evenly over the remaining part of the area.
4. Continue to use every day.

WARNINGS

For external use only.For external use only Keep away from fire and flame

KEEP OUT OF REACH OF CHILDREN

If swallowed, get medical help or contact a Poison Control Center right away.

DO NOT USE

You are under 18 years old. Do not use this product on infants and children. If your skin is red, swollen, inflamed, infected, itchy or painful, do not use it.
You are currently taking other medications to treat your illness. If you have heart disease, consult your doctor before using it.

STOP USE

Chest pain, rapid heart beat, faintness, or dizziness occurs sudden, unexplained weight gain occurs,your hands or feet swell.

INACTIVE INGREDIENT

WATER、GLYCERIN、PANTHENOL、CETEARYL ALCOHOL、VITIS VINIFERA (GRAPE) SEED OIL、SIMMONDSIA CHINENSIS (JOJOBA) SEED OIL、CAMELLIA JAPONICA SEED OIL、TOCOPHEROL、ESTRIOL、SOY ISOFLAVONES、HYALURONIC ACID、BUTYROSPERMUM PARKII (SHEA) OIL

DOSAGE AND ADMINISTRATION

Twice each day, (1ml)each time. 15 days supply